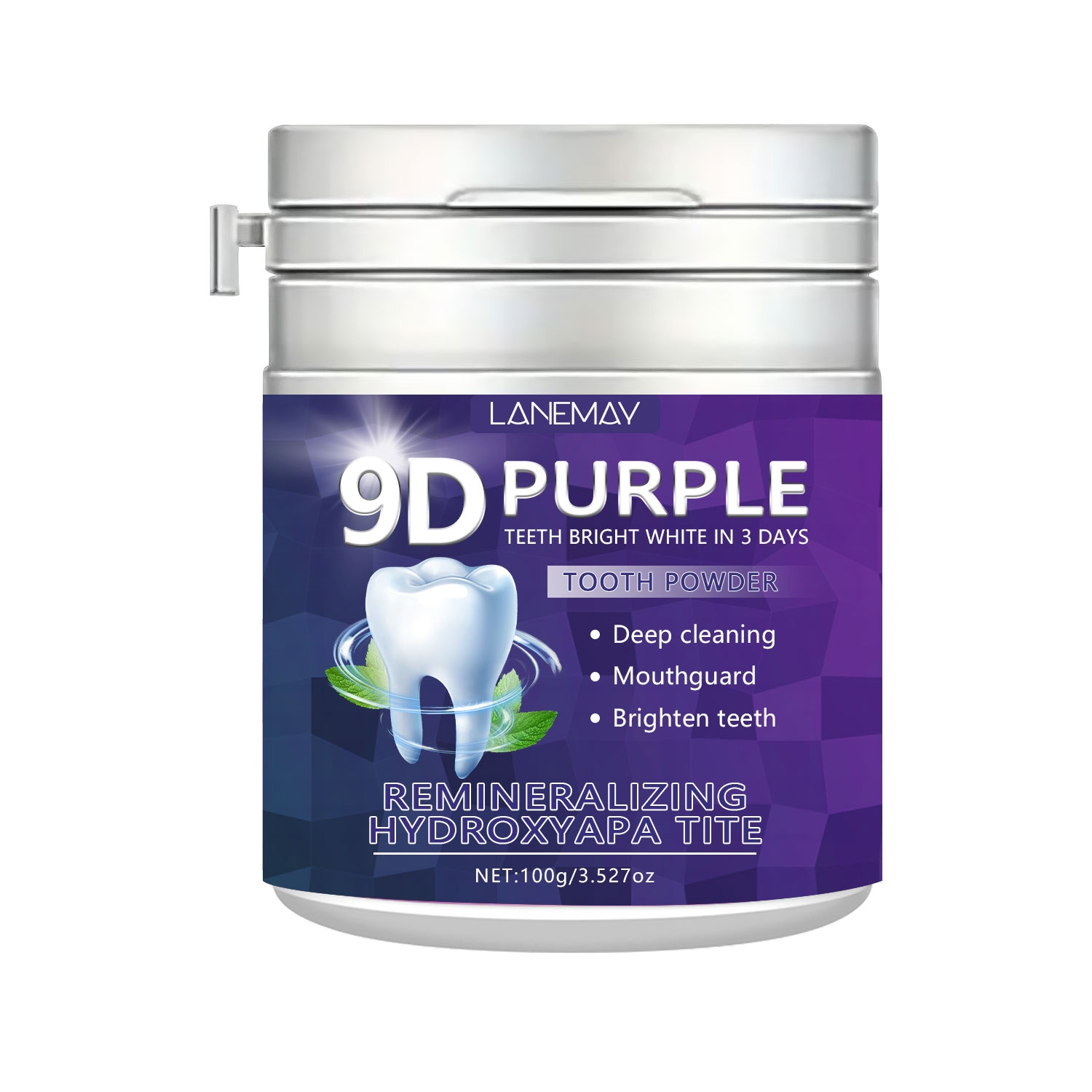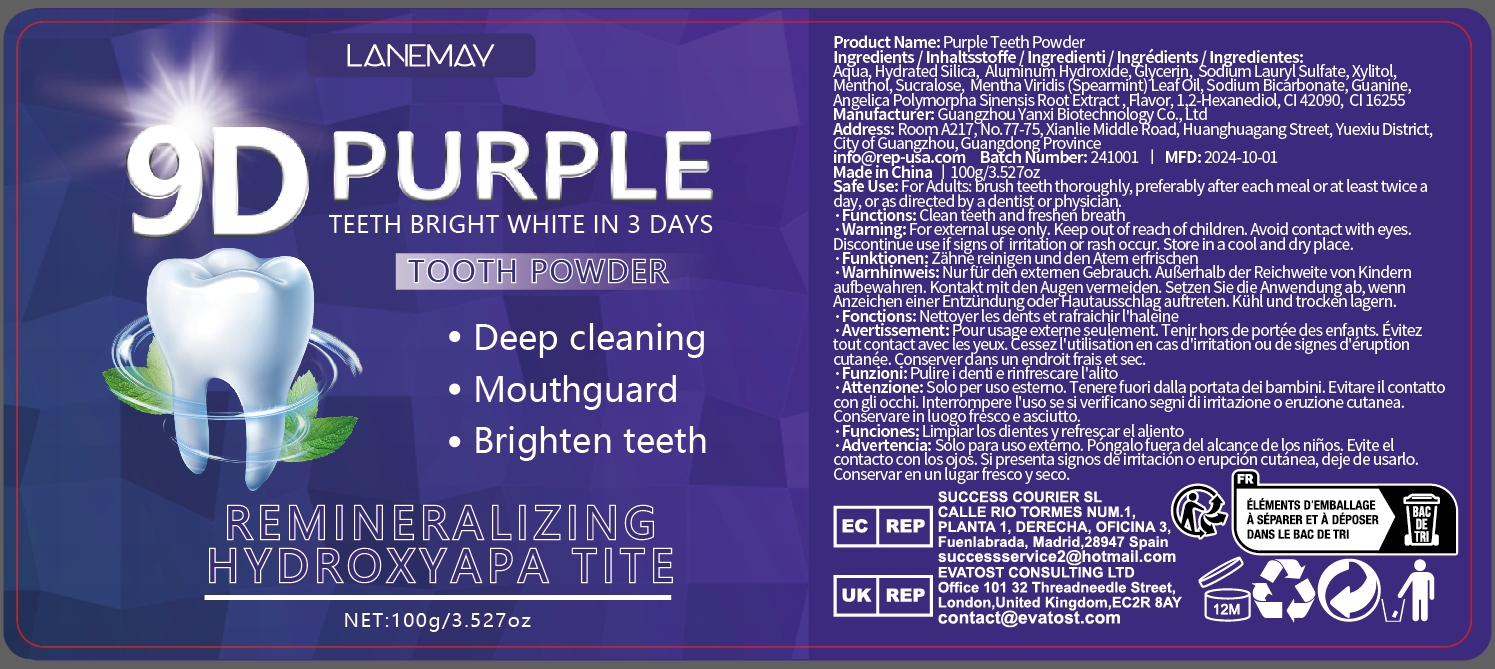 DRUG LABEL: Purple Teeth Powder
NDC: 84025-266 | Form: POWDER
Manufacturer: Guangzhou Yanxi Biotechnology Co., Ltd
Category: otc | Type: HUMAN OTC DRUG LABEL
Date: 20241121

ACTIVE INGREDIENTS: ALUMINUM HYDROXIDE 3 mg/100 g; HYDRATED SILICA 5 mg/100 g
INACTIVE INGREDIENTS: WATER

DOSAGE AND ADMINISTRATION

For Adults:brush teeth thoroughly,preferably after each meal or at least twice a day,or as directed by o dentist or physician

WARNINGS

Keep out of children

INACTIVE INGREDIENT

Aqua

INDICATIONS AND USAGE

For daily teeth care

Keep out of children

PURPOSE

Deep cleaning teeth